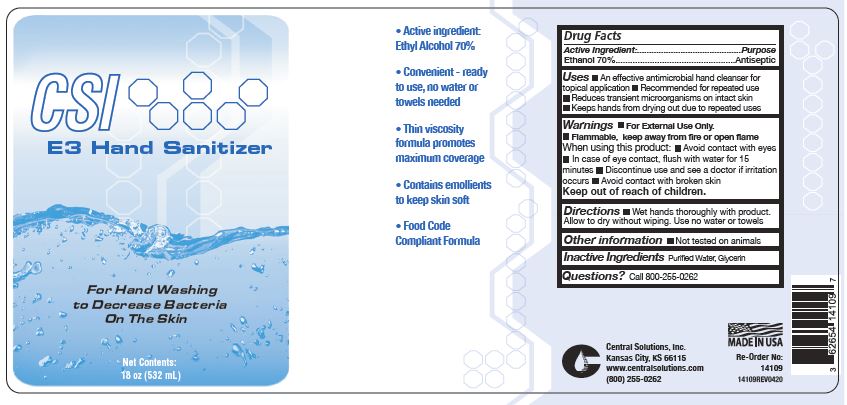 DRUG LABEL: CSI E3 Hand Sanitizer
NDC: 62654-139 | Form: LIQUID
Manufacturer: Central Solutions Inc
Category: otc | Type: HUMAN OTC DRUG LABEL
Date: 20241209

ACTIVE INGREDIENTS: ALCOHOL 70 mL/100 mL
INACTIVE INGREDIENTS: GLYCERIN; WATER

CSI E3 Hand Sanitizer 62654-139

Active Ingredient

Ethanol 70%

Purpose

Antiseptic

Uses

An effective antimicrobial hand cleanser for topical application

Recommended for repeated use

Reduces transient microorganisms on intact skin

Keep hands from drying out due to repeated uses

Warnings

For External Use Only.

Flammable, keep away from fire or opem flame

When using this product:

Avoid contact with eyes

In case of eye contact, flush with water for 15 minutes

STOP USE

Discontinue use and see a doctor if irritation occurs

Avoid contact with broken skin

Keep out of reach of children.

Directions

Wet hands thoroughly with product.

Allow to dry without wiping.

Use no water or towels

Other information

Not tested on animals

Inactive Ingredients

Purified Water, Glycerin

Questions?

Call 800-255-0262

PACKAGE LABEL

CSI

E3 Hand Sanitizer

For Hand Washing

to Decrease Bacteria

On The Skin

Net Contents:

18 oz (532 mL)